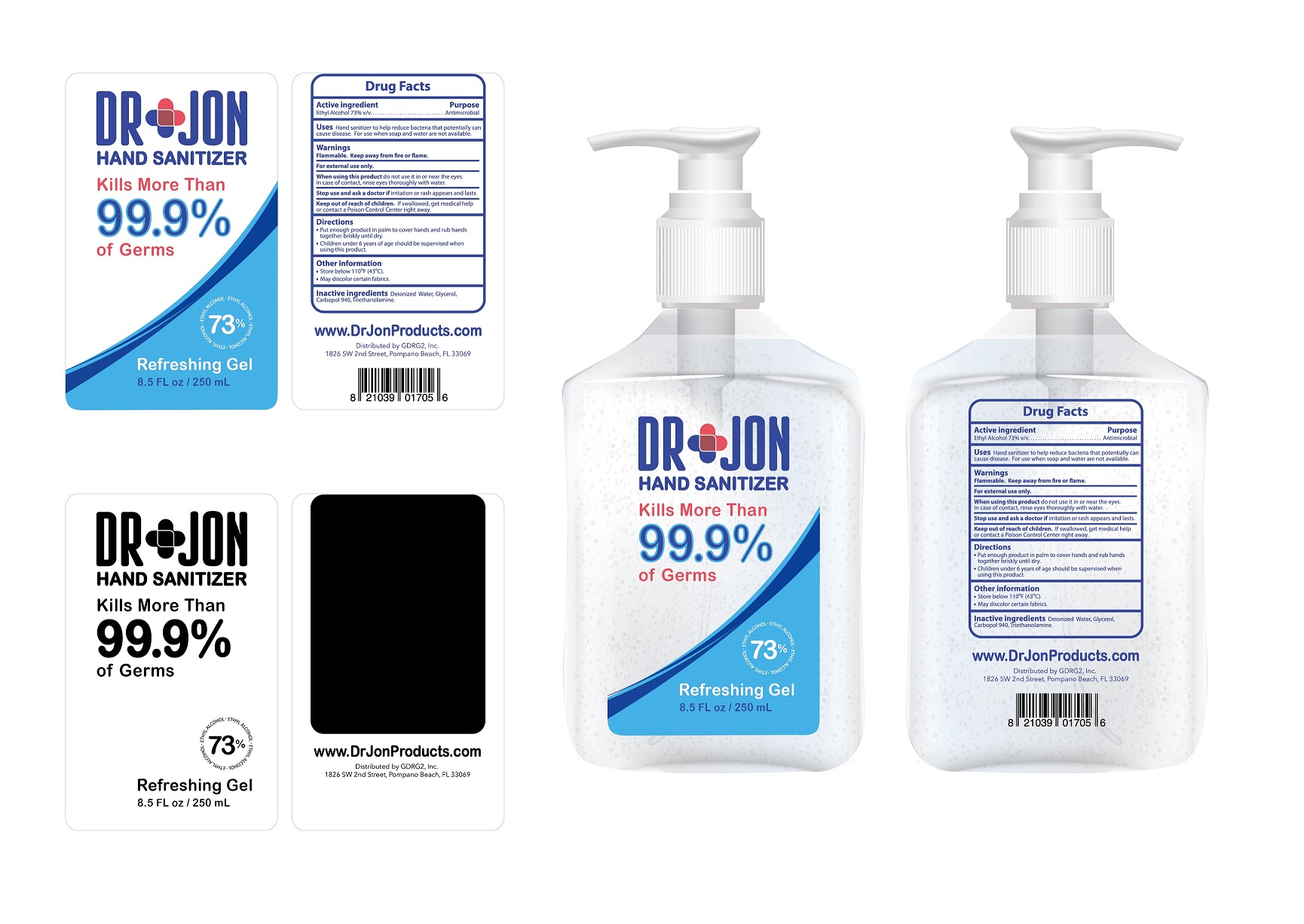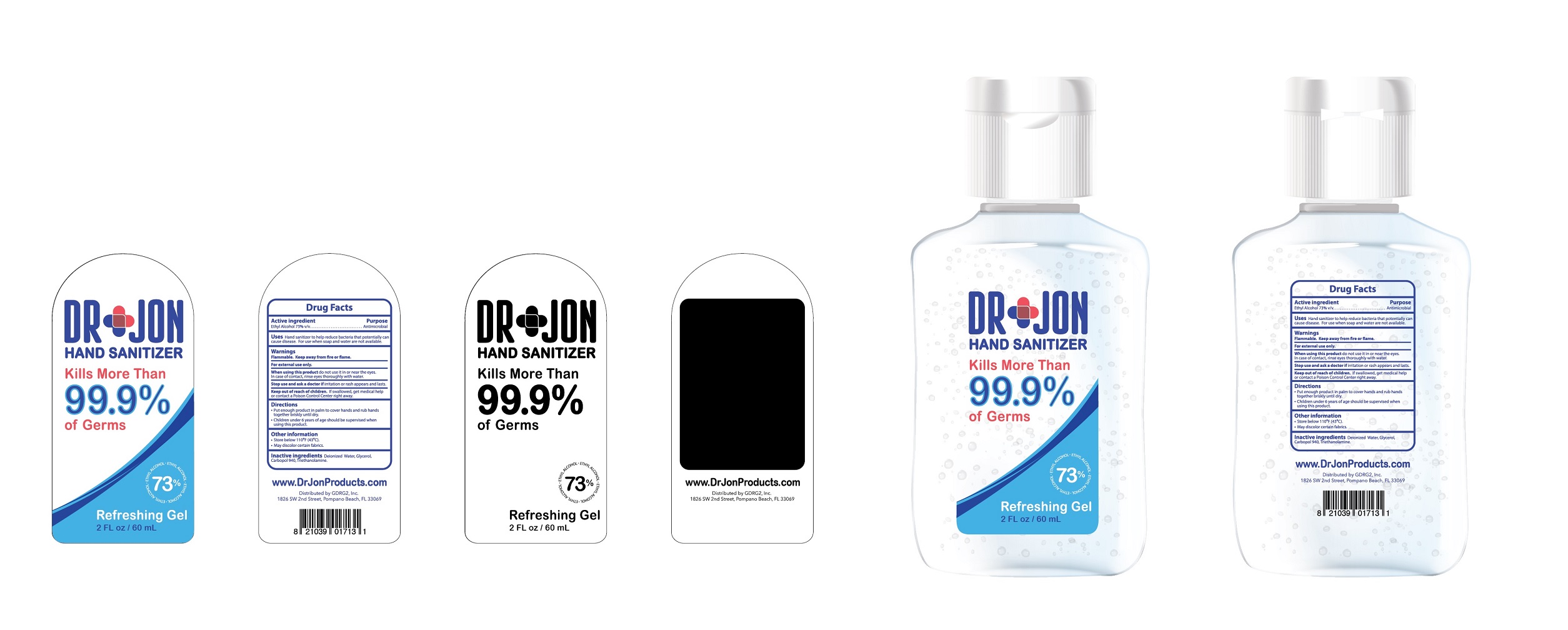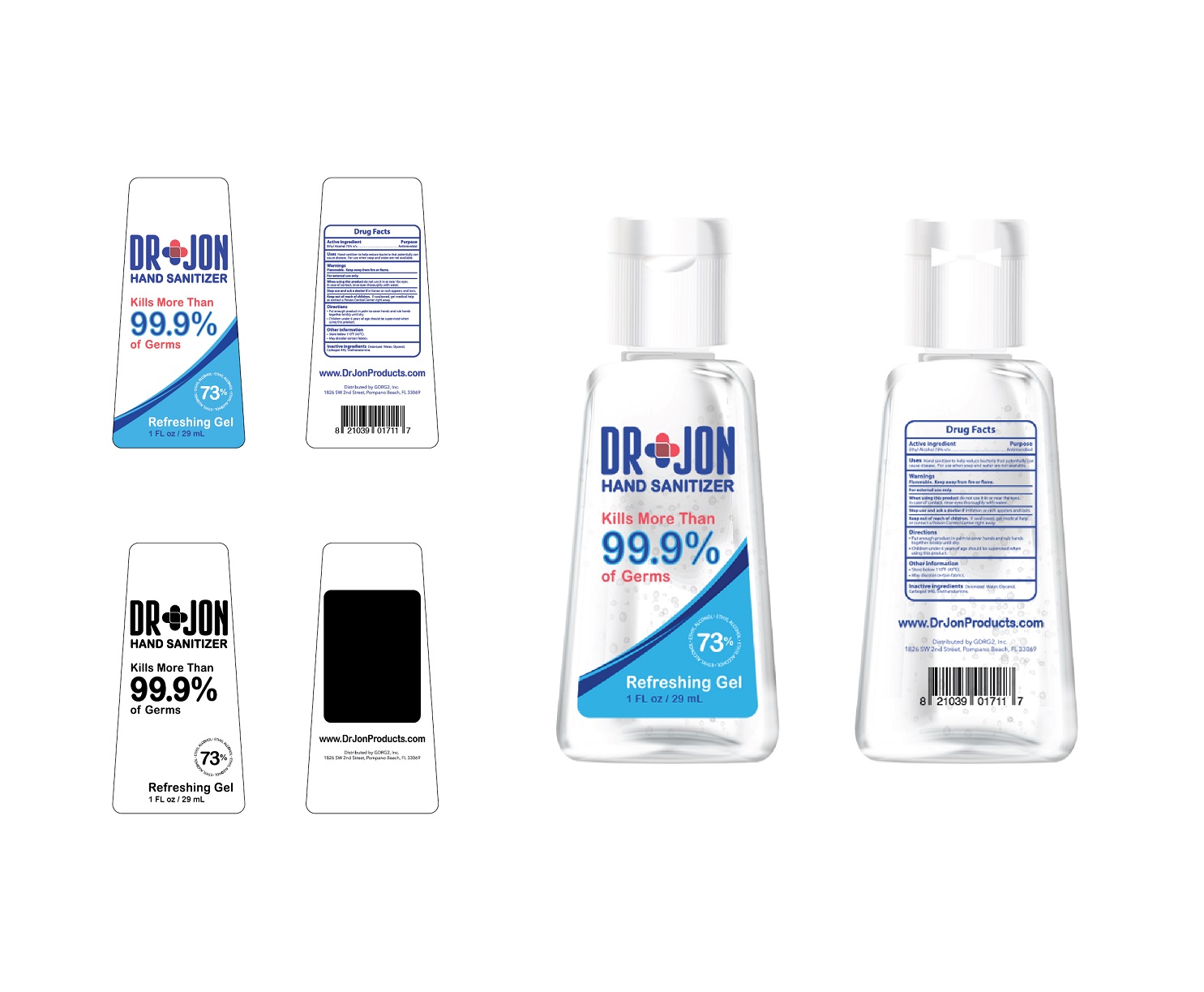 DRUG LABEL: Hand Sanitizer
NDC: 76999-7131 | Form: GEL
Manufacturer: GDRG2, Inc.
Category: otc | Type: HUMAN OTC DRUG LABEL
Date: 20200428

ACTIVE INGREDIENTS: ALCOHOL 40.8 mL/60 mL
INACTIVE INGREDIENTS: GLYCERIN 0.6 mL/60 mL; CARBOMER 940 0.27 mL/60 mL; CUPRIC BIS(TRIETHANOLAMINE) 0.15 mL/60 mL; WATER 15.18 mL/60 mL

This is a hand sanitizer manufactured according to the Temporary Policy for Preparation of Certain Alcohol-Based Hand Sanitizer Products During the Public Health Emergency (CoViD-19); Guidance for Industry.

The hand sanitizer is manufactured using only the following United States Pharmacopoeia (USP) grade ingredients in the preparation of the product (percentage in final product formulation) consistent with World Health Organization (WHO) recommendations:

1. Alcohol (ethanol) (USP or Food Chemical Codex (FCC) grade) (73%, volume/volume (v/v)) in an aqueous solution denatured according to Alcohol and Tobacco Tax and Trade Bureau regulations in 27 CFR part 20.
2. Glycerol (1.00% v/v).
3. Carbopol 940 (0.45% v/v).
4. Triethanolamine (0.25% v/v).
5. Sterile deionized water.

The firm does not add other active or inactive ingredients. Different or additional ingredients may impact the quality and potency of the product.

Active Ingredient(s)

Ethyl Alcohol 73% v/v. Purpose: Antiseptic

Purpose

Antimicrobial

Uses

Hand Sanitizer to help reduce bacteria that potentially can cause disease. For use when soap and water are not available.

Warnings

Flammable. Keep away from heat or flame. For external use only.

Do not use

- in or near the eyes

When using this product do not use it in or near the eyes. In case of contact with eyes, rinse eyes thoroughly with water.
Stop use and ask a doctor if irritation or rash appears and lasts.
Keep out of reach of children. If swallowed, get medical help or contact a Poison Control Center right away.

Stop use and ask a doctor if irritation or rash appears and lasts.

Keep out of reach of children. If swallowed, get medical help or contact a Poison Control Center right away.

Directions

- Put enough product in palm to cover hands and rub hands together briskley until dry.
- Children under 6 years of age should be supervised when using this product.

Other information

- Store below 110F (43C)
- May discolor certain fabrics

Inactive ingredients

Deionized Water, Glycerol, Carbopol 940, Triethanolamine

Package Label - Principal Display Panel

29 mL NDC: 76999-7117-6
60 mL NDC: 76999-7094-5
250 mL NDC: 76999-7056-3